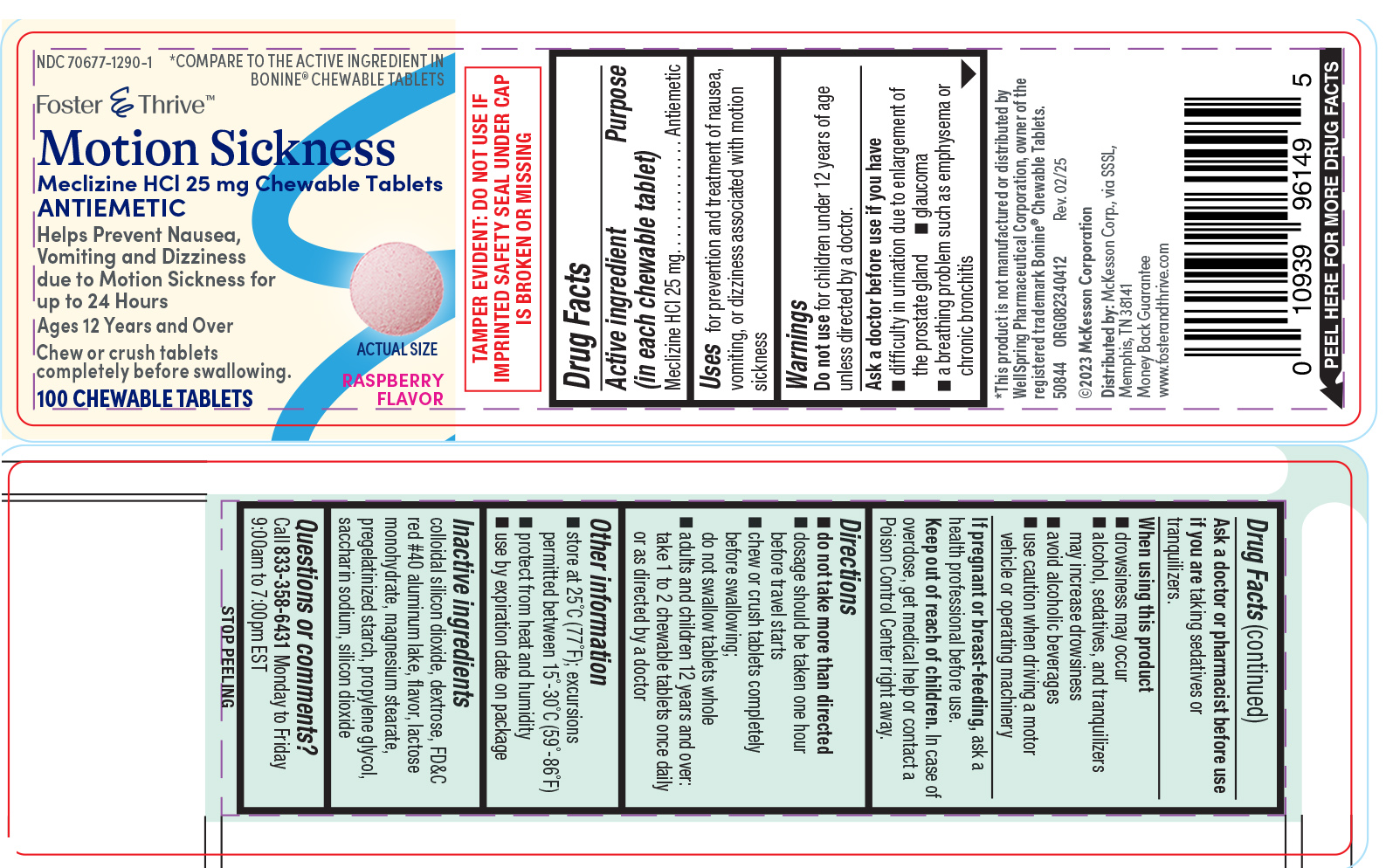 DRUG LABEL: Motion Sickness
NDC: 70677-1290 | Form: TABLET, CHEWABLE
Manufacturer: Strategic Sourcing Services LLC
Category: otc | Type: HUMAN OTC DRUG LABEL
Date: 20250521

ACTIVE INGREDIENTS: MECLIZINE HYDROCHLORIDE 25 mg/1 1
INACTIVE INGREDIENTS: SILICON DIOXIDE; DEXTROSE, UNSPECIFIED FORM; FD&C RED NO. 40 ALUMINUM LAKE; LACTOSE MONOHYDRATE; MAGNESIUM STEARATE; STARCH, CORN; PROPYLENE GLYCOL; SACCHARIN SODIUM

Foster and Thrive 44-404A

Active ingredient (in each chewable tablet)

Meclizine HCl 25 mg

Purpose

Antiemetic

Uses

for prevention and treatment of nausea, vomiting, or dizziness associated with motion sickness

Warnings

Do not use

for children under 12 years of age unless directed by a doctor.

Ask a doctor before use if you have

- glaucoma
- difficulty in urination due to enlargement of the prostate gland
- a breathing problem such as emphysema or chronic bronchitis

Ask a doctor or pharmacist before use if you are

taking sedatives or tranquilizers.

When using this product

- drowsiness may occur
- alcohol, sedatives, and tranquilizers may increase drowsiness
- avoid alcoholic beverages
- use caution when driving a motor vehicle or operating machinery

If pregnant or breast-feeding,

ask a health professional before use.

Keep out of reach of children.

In case of overdose, get medical help or contact a Poison Control Center right away.

Directions

- do not take more than directed
- dosage should be taken one hour before travel starts
- chew or crush tablets completely before swallowing; do not swallow tablets whole
- adults and children 12 years and over: take 1 to 2 chewable tablets once daily or as directed by a doctor

Other information

- TAMPER EVIDENT: DO NOT USE IF OUTER PACKAGE IS OPENED OR BLISTER IS TORN OR BROKEN
- store at 25ºC (77ºF); excursions permitted between 15º-30ºC (59º-86ºF)
- protect from heat and humidity
- see end flap for expiration date and lot number

Inactive ingredients

colloidal silicon dioxide, dextrose, FD&C red #40 aluminum lake, flavor, lactose monohydrate, magnesium stearate, pregelatinized starch, propylene glycol, saccharin sodium, silicon dioxide

Questions or comments?

1-800-426-9391

Principal Display Panel

NDC 70677-1290-1

*COMPARE TO THE ACTIVE INGREDIENT IN
BONINE® CHEWABLE TABLETS

Foster & Thrive

Motion Sickness
Meclizine HCl 25 mg Chewable Tablets

ANTIEMETIC

Helps Prevent Nausea,
Vomiting and Dizziness
due to Motion Sickness for
up to 24 Hours
Ages 12 Years and Over

Chew or crush tablets
completely before swallowing.

100 CHEWABLE TABLETS

RASPBERRY
FLAVOR

TAMPER EVIDENT: DO NOT USE IF
IMPRINTED SAFETY SEAL UNDER CAP
IS BROKEN OR MISSING

*This product is not manufactured or distributed by
WellSpring Pharmaceutical Corporation, owner of the
registered trademark Bonine® Chewable Tablets.

50844 ORG082340412 Rev. 02/25

©2023 McKesson Corporation

Distributed by: McKesson Corp., via SSSL,
Memphis, TN 38141
Money Back Guarantee
www.fosterandthrive.com

Foster and thrive 44-404A